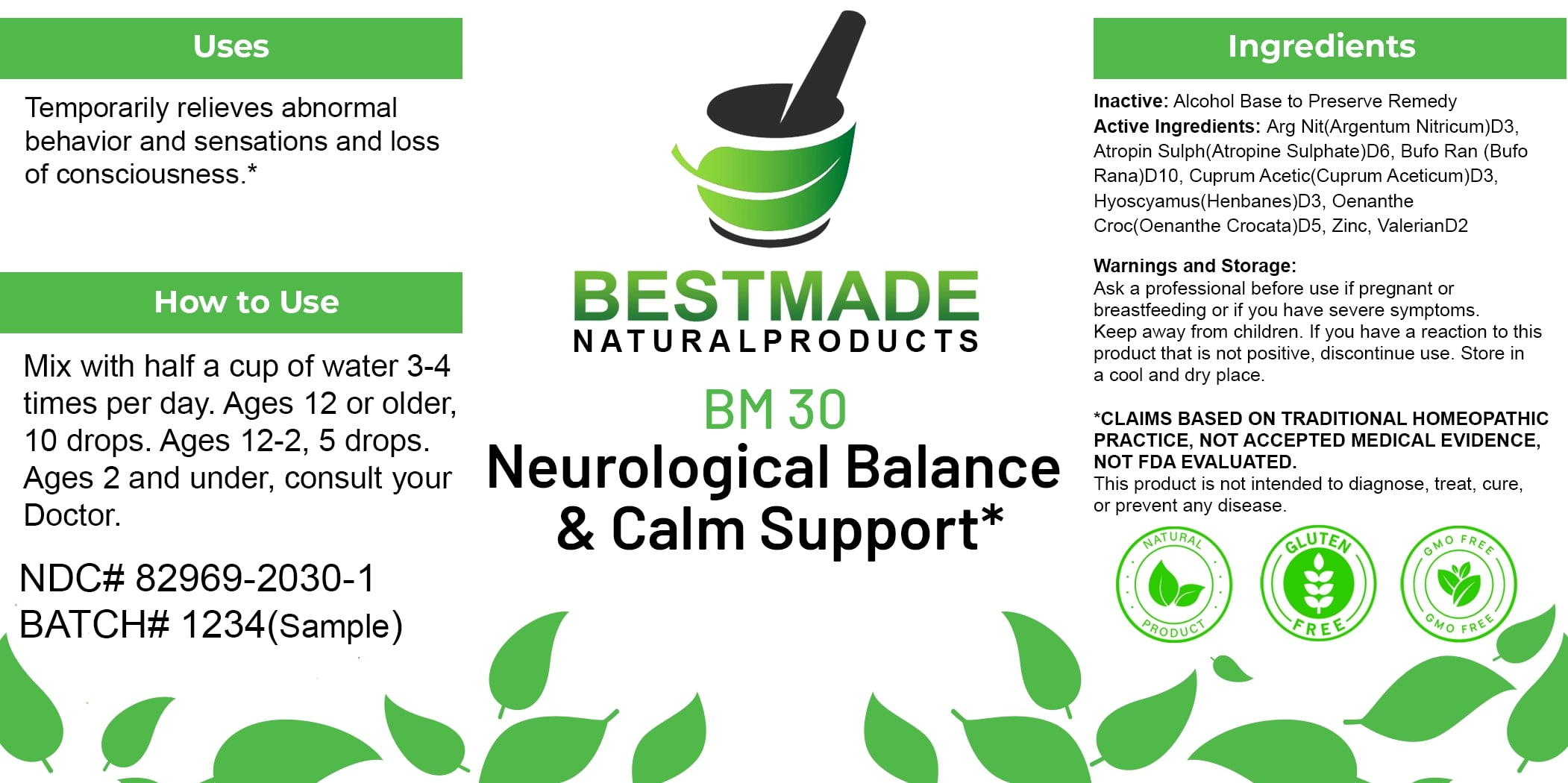 DRUG LABEL: Bestmade Natural Products BM30
NDC: 82969-2030 | Form: LIQUID
Manufacturer: Bestmade Natural Products
Category: homeopathic | Type: HUMAN OTC DRUG LABEL
Date: 20250123

ACTIVE INGREDIENTS: ATROPINE SULFATE 30 [hp_C]/30 [hp_C]; SILVER NITRATE 30 [hp_C]/30 [hp_C]; BUFO BUFO CUTANEOUS GLAND 30 [hp_C]/30 [hp_C]; CUPRIC ACETATE 30 [hp_C]/30 [hp_C]; OENANTHE CROCATA ROOT 30 [hp_C]/30 [hp_C]; ZINC 30 [hp_C]/30 [hp_C]; VALERIAN 30 [hp_C]/30 [hp_C]
INACTIVE INGREDIENTS: ALCOHOL 30 [hp_C]/30 [hp_C]

BM30

DOSAGE AND ADMINISTRATION

How to Use

Mix with half a cup of water 3-4 times per day. Ages 12 or older, 10 drops. Ages 12-2, 5 drops. Ages 2 and under, consult your Doctor.

INACTIVE INGREDIENT

Ingredients

Inactive: Alcohol Base to Preserve Remedy

Uses

Temporarily relieves abnormal behavior and sensations and loss of consciousness.*

*CLAIMS BASED ON TRADITIONAL HOMEOPATHIC PRACTICE, NOT ACCEPTED MEDICAL EVIDENCE, NOT FDA EVALUATED.

This product is not intended to diagnose, treat, cure, or prevent any disease.

Active Ingredients:

Arg Nit(Argentum Nitricum)D3, Atropin Sulph(Atropine Sulphate)D6, Bufo Ran(Bufo Rana)D10, Cuprum Acetic(Cuprum Aceticum)D3, Hyoscyamus(Henbanes)D3, Oenanthe Croc(Oenanthe Crocata)D5, Zinc, ValerianD2

KEEP OUT OF REACH OF CHILDREN

Warnings and Storage:

Ask a professional before use if pregnant or breastfeeding or if you have severe symptoms. Keep away from children. If you have a reaction to this product that is not positive, discontinue use. Store in a cool and dry place.

Uses

Temporarily relieves abnormal behavior and sensations and loss of consciousness.*

*CLAIMS BASED ON TRADITIONAL HOMEOPATHIC PRACTICE, NOT ACCEPTED MEDICAL EVIDENCE, NOT FDA EVALUATED.

This product is not intended to diagnose, treat, cure, or prevent any disease.

Warnings and Storage:

Ask a professional before use if pregnant or breastfeeding or if you have severe symptoms. Keep away from children. If you have a reaction to this product that is not positive, discontinue use. Store in a cool and dry place.

*CLAIMS BASED ON TRADITIONAL HOMEOPATHIC PRACTICE, NOT ACCEPTED MEDICAL EVIDENCE, NOT FDA EVALUATED.

This product is not intended to diagnose, treat, cure, or prevent any disease.

Entire package label